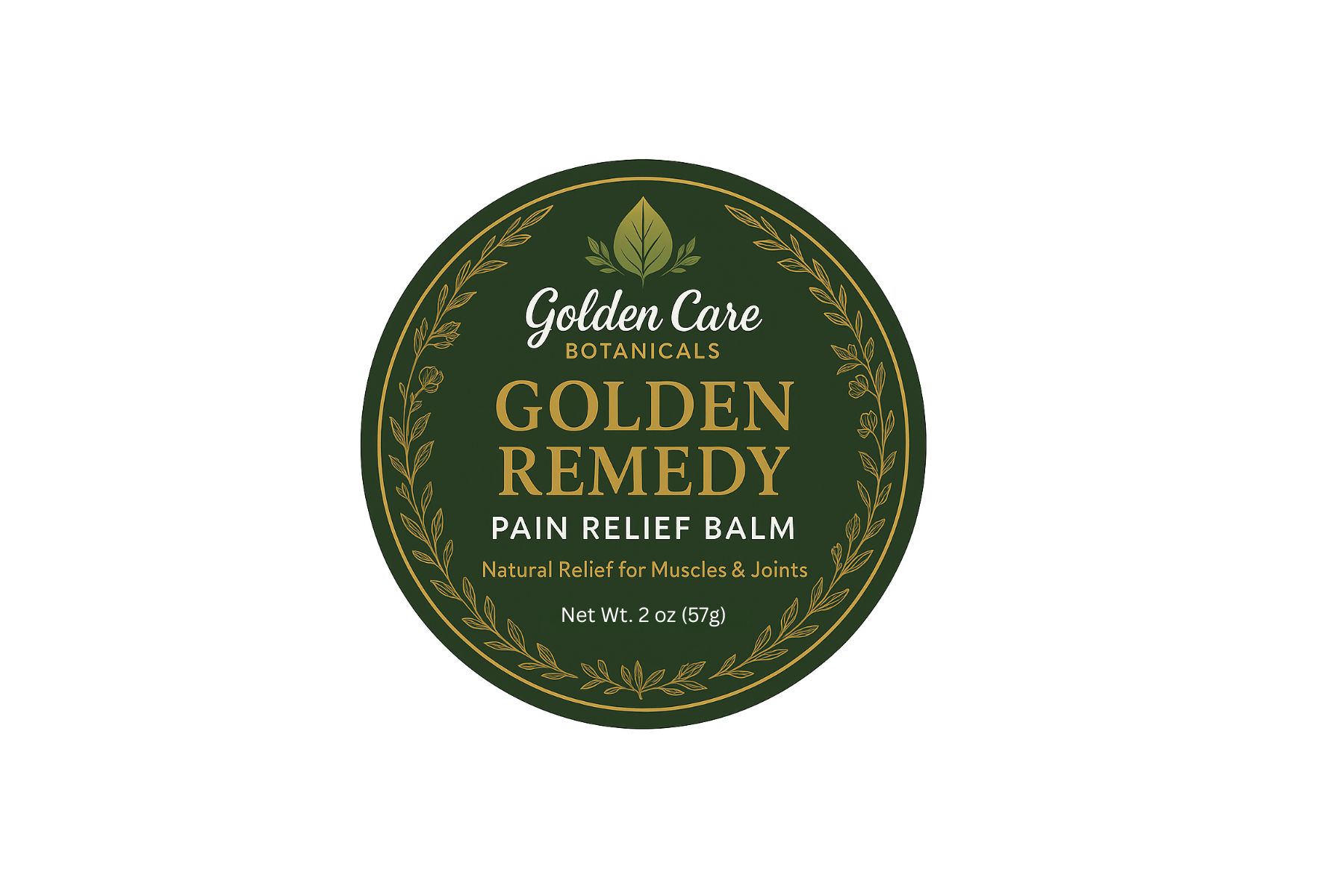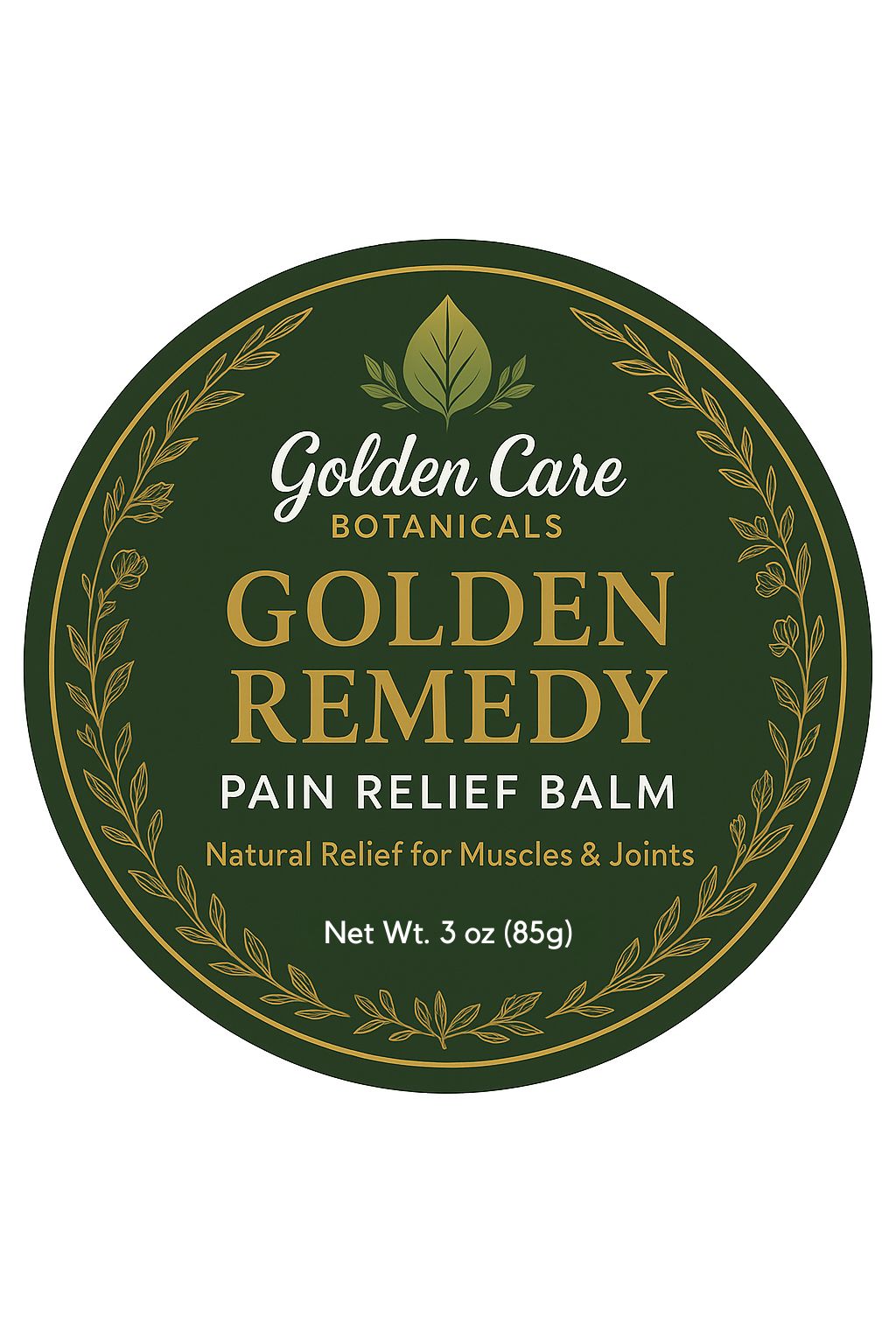 DRUG LABEL: Golden Remedy Pain Relief Balm
NDC: 87037-001 | Form: SALVE
Manufacturer: GOLDEN CARE BOTANICALS LLC
Category: otc | Type: HUMAN OTC DRUG LABEL
Date: 20250815

ACTIVE INGREDIENTS: MENTHOL 4.8 g/4.8 g; CAMPHOR (NATURAL) 4.8 g/4.8 g
INACTIVE INGREDIENTS: BEESWAX; GINGER OIL; COCOA BUTTER; AVOCADO OIL; SHEA BUTTER; MANGIFERA INDICA (MANGO) SEED BUTTER; AVOCADO SEED; HELICHRYSUM GYMNOCEPHALUM WHOLE; FRANKINCENSE; .ALPHA.-TOCOPHEROL ACETATE, D-

PURPOSE

Topical analgesic for temporary relief of minor aches and pain of muscles and joints associated with backach, arthritis, strains, brusies, and sprains

Do not use on open wounds, broken skin, or with a heating pad

Stop use and ask a doctor if: condition worsens, or symptoms persist for more than 7 days.

WARNINGS

For external use only

INACTIVE INGREDIENT

Inactive ingredients: beeswax, avocado oil, shea butter, cocoa butter, mango butter, menthol crystals, avocado seed powder, camphor, helichrysum, frankincense, ginger oil, vitamin e

Directions:
Adults and children 12 years and over: Apply to the affected area not more than 3 to 4 times daily.

Route of Administration:Topical (external) use only

INDICATIONS AND USAGE

Route of Administration:Topical

KEEP OUT OF REACH OF CHILDREN

If swallowed, seek immediate medical attention or contact Poison Control